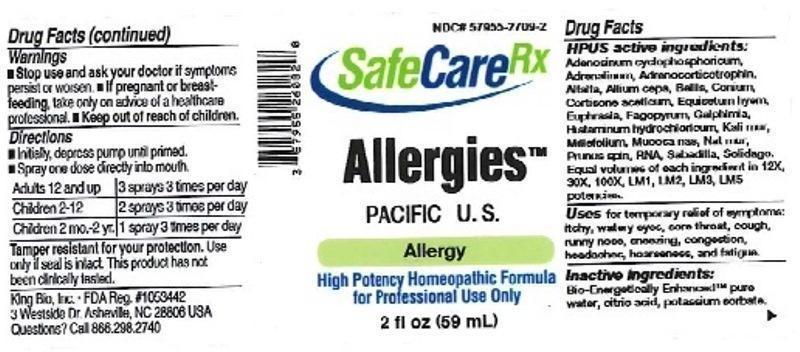 DRUG LABEL: Allergies Pacific U.S.
NDC: 57955-2709 | Form: LIQUID
Manufacturer: King Bio Inc.
Category: homeopathic | Type: HUMAN OTC DRUG LABEL
Date: 20150812

ACTIVE INGREDIENTS: ADENOSINE CYCLIC PHOSPHATE 12 [hp_X]/59 mL; EPINEPHRINE 12 [hp_X]/59 mL; CORTICOTROPIN 12 [hp_X]/59 mL; ALFALFA 12 [hp_X]/59 mL; ONION 12 [hp_X]/59 mL; BELLIS PERENNIS 12 [hp_X]/59 mL; CONIUM MACULATUM FLOWERING TOP 12 [hp_X]/59 mL; CORTISONE ACETATE 12 [hp_X]/59 mL; EQUISETUM HYEMALE 12 [hp_X]/59 mL; EUPHRASIA STRICTA 12 [hp_X]/59 mL; FAGOPYRUM ESCULENTUM 12 [hp_X]/59 mL; GALPHIMIA GLAUCA FLOWERING TOP 12 [hp_X]/59 mL; HISTAMINE DIHYDROCHLORIDE 12 [hp_X]/59 mL; POTASSIUM CHLORIDE 12 [hp_X]/59 mL; ACHILLEA MILLEFOLIUM 12 [hp_X]/59 mL; SUS SCROFA NASAL MUCOSA 12 [hp_X]/59 mL; SODIUM CHLORIDE 12 [hp_X]/59 mL; PRUNUS SPINOSA FLOWER BUD 12 [hp_X]/59 mL; SACCHAROMYCES CEREVISIAE RNA 12 [hp_X]/59 mL; SCHOENOCAULON OFFICINALE SEED 12 [hp_X]/59 mL; SOLIDAGO VIRGAUREA FLOWERING TOP 12 [hp_X]/59 mL
INACTIVE INGREDIENTS: WATER; ANHYDROUS CITRIC ACID; POTASSIUM SORBATE

Allergies:Pacific U.S.

ACTIVE INGREDIENT

Drug Facts__________________________________________________________________________________________________________

HPUS active ingredients: Adenosinum cyclophosphoricum, Adrenalinum, Adrenocorticotrophin, Alfalfa, Allium cepa, Bellis perennis, Conium maculatum, Cortisone aceticum, Equisetum hyemale, Euphrasia officinalis, Fagopyrum esculentum, Galphimia glauca, Histaminum hydrochloricum, Kali muriaticum, Millefolium, Mucosa nasalis suis, Natrum muriaticum, Prunus spinosa, RNA, Sabadilla, Solidago virgaurea. Equal volumes of each ingredient in 12X, 30X, 100X, LM1, LM2, LM3, LM5 potencies.

INDICATIONS AND USAGE

Uses for temporary relief of symptoms: itchy, watery eyes, sore throat, cough, runny nose, sneezing, congestion, headache, hoarseness, and fatigue.

Inactive Ingredients:

Bio-Energetically Enhanced™ pure water, citric acid and potassium sorbate.

Warnings

- Stop use and ask your doctor if symptoms persist or worsen.
- If pregnant or breast-feeding, take only on advice of a healthcare professional.

- Keep out of reach of children.

Directions

- Initially, depress pump until primed.
- Spray one dose directly into mouth.
- Adults 12 and up: 3 sprays 3 times per day.
- Children 2-12: 2 sprays 3 times per day.
- Children 2 mo-2yr: 1 sprary 3 times per day.

OTHER SAFETY INFORMATION

Tamper resistant for your protection. Use only if seal is intact. This product has not been clinically tested.

PURPOSE

Uses for temporary relief of symptoms:

- itchy, watery eyes
- sore throat
- cough
- runny nose
- sneezing
- congestion
- headache
- hoarseness
- fatigue